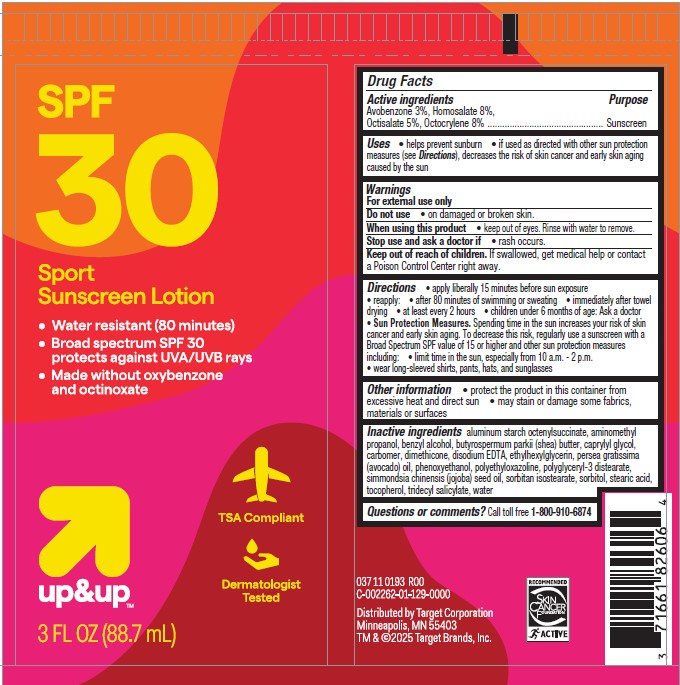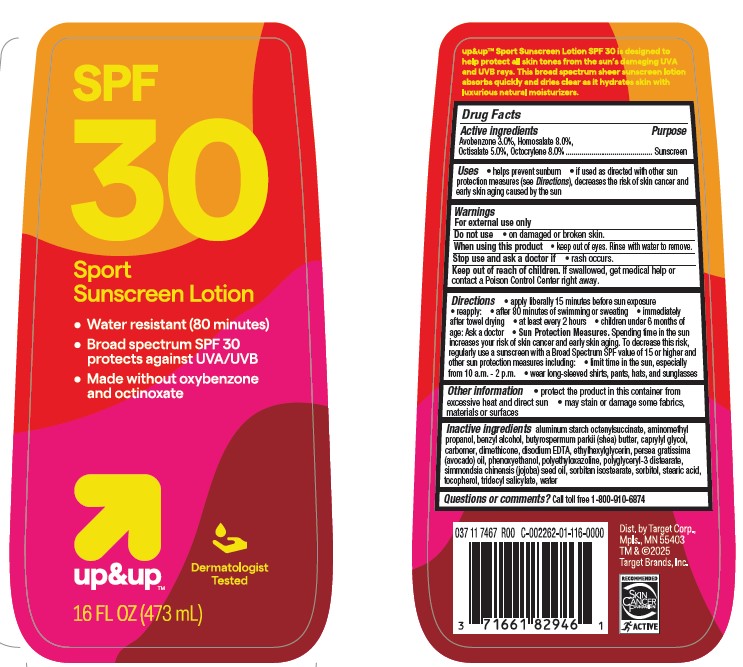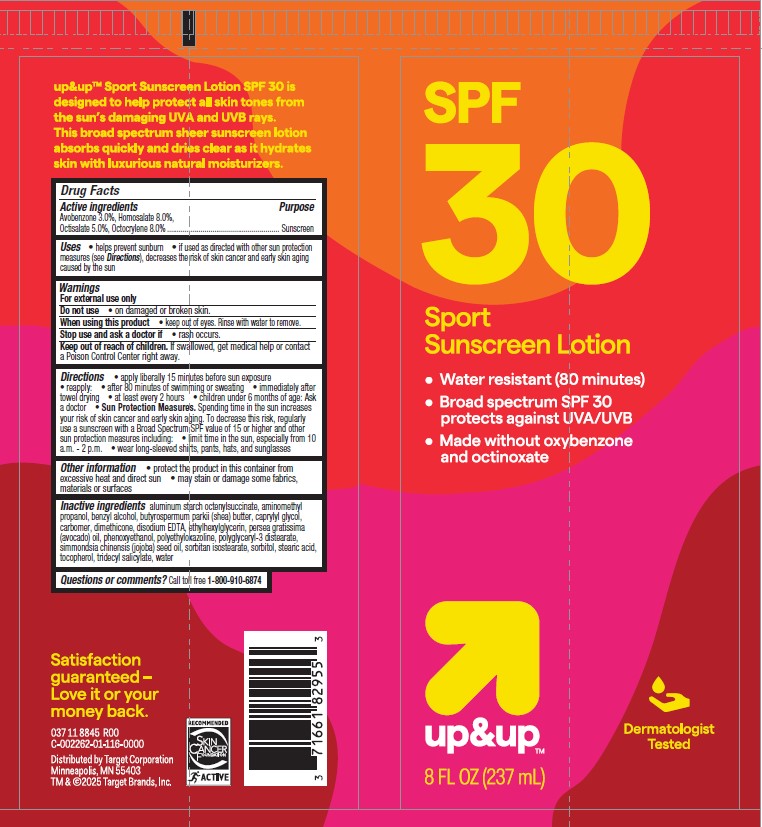 DRUG LABEL: Target Up and Up SPF 30 Sport Sunscreen
NDC: 82442-006 | Form: LOTION
Manufacturer: TARGET CORPORATION
Category: otc | Type: HUMAN OTC DRUG LABEL
Date: 20240925

ACTIVE INGREDIENTS: AVOBENZONE 30 mg/1 mL; HOMOSALATE 80 mg/1 mL; OCTOCRYLENE 80 mg/1 mL; OCTISALATE 50 mg/1 mL
INACTIVE INGREDIENTS: HEXAMETHYLDISILOXANE; CAPRYLYL GLYCOL; .ALPHA.-TOCOPHEROL, DL-; AVOCADO OIL; SHEA BUTTER; ETHYLHEXYLGLYCERIN; JOJOBA OIL; WATER; EDETATE DISODIUM; PHENOXYETHANOL; STEARIC ACID; POLYGLYCERYL-3 DISTEARATE; SORBITOL; ALUMINUM STARCH OCTENYLSUCCINATE; SORBITAN ISOSTEARATE; POLYETHYLOXAZOLINE (5000 MW); BENZYL ALCOHOL; CARBOMER INTERPOLYMER TYPE A (ALLYL SUCROSE CROSSLINKED); TRIDECYL SALICYLATE; AMINOMETHYLPROPANOL

Target Up and Up SPF 30 Sport Sunscreen Lotion

Active ingredients

Avobenzone 3%
Homosalate 8%

Octisalate 5%
Octocrylene 8%

Purpose

Sunscreen

Uses

• helps prevent sunburn
• if used as directed with other sun protection measures (see Directions), decreases the risk of skin cancer and early skin aging caused by the sun

Warnings

For external use only

Do not use

• on damaged or broken skin.

When using this product

• keep out of eyes. Rinse with water to remove

Stop use and ask a doctor if

• rash occurs

Keep out of reach of children

If swallowed, get medical help or contact a Poison Control Center right away.

Directions

• apply liberally 15 minutes before sun exposure
• reapply:
• after 80 minutes of swimming or sweating
• immediately after towel drying
• at least every 2 hours
• children under 6 months of age: Ask a doctor
• Sun Protection Measures. Spending time in the sun increases your risk of skin cancer and early skin aging. To decrease this risk, regularly use a sunscreen with a Broad Spectrum SPF value of 15 or higher and other sun protection measures including:
• limit time in the sun, especially from 10 a.m. - 2 p.m.

• wear long-sleeved shirts, pants, hats, and sunglasses

Other information

• protect the product in this container from excessive heat and direct sun
• may stain or damage some fabrics, materials or surfaces

Inactive ingredients

aluminum starch octenylsuccinate, aminomethyl
propanol, benzyl alcohol, butyrospermum parkii (shea) butter, caprylyl glycol,
carbomer, dimethicone, disodium EDTA, ethylhexylglycerin, persea gratissima
(avocado) oil, phenoxyethanol, polyethyloxazoline, polyglyceryl-3 distearate,
simmondsia chinensis (jojoba) seed oil, sorbitan isostearate, sorbitol, stearic acid,
tocopherol, tridecyl salicylate, water